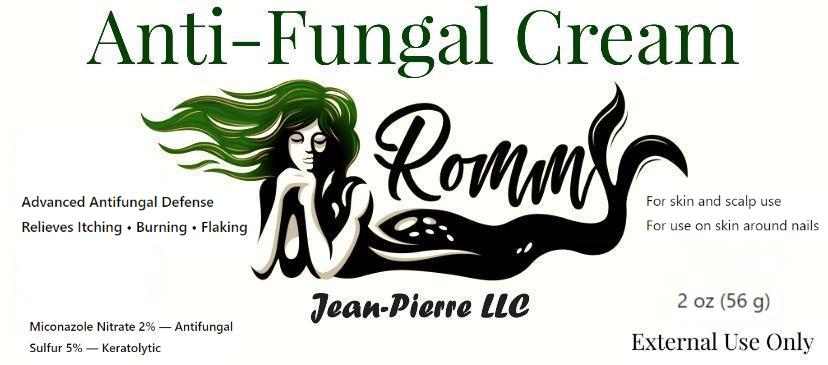 DRUG LABEL: RoMMY Jean-Pierre LLC Anti-fungal Cream
NDC: 87306-126 | Form: CREAM
Manufacturer: RoMMY Jean-Pierre LLC
Category: otc | Type: HUMAN OTC DRUG LABEL
Date: 20260208

ACTIVE INGREDIENTS: CAMPHOR (SYNTHETIC) 1 g/100 g; MENTHOL 1 g/100 g; MICONAZOLE NITRATE 2 g/100 g; SULFUR 5 g/100 g
INACTIVE INGREDIENTS: ALPHA-TOCOPHEROL ACETATE; PETROLATUM; THYMOL; PEPPERMINT OIL; CARTHAMUS TINCTORIUS (SAFFLOWER) SEED OIL; ALOE BARBADENSIS LEAF JUICE

Active ingredients

Miconazole nitrate 2%
Sulfur 5%
Camphor 1%
Menthol 1%

Purpose

Antifungal
Keratolytic
External Analgesic

INDICATIONS AND USAGE

Cures most athlete’s foot, jock itch, and ringworm
Relieves itching, burning, cracking, and scaling associated with these conditions
Helps relieve itching and discomfort associated with minor skin irritation
Helps loosen and remove excessive dead skin and flakes

WARNINGS

For external use only

Do not use on children under 2 years of age unless directed by a doctor

When using this product avoid contact with eyes
do not apply to broken or severely irritated skin

Stop use and ask a doctor if:
irritation occurs
condition worsens
symptoms persist for more than 4 weeks

Keep out of reach of children.
If swallowed, get medical help or contact a Poison Control Center right away.

Keep out of reach of children.
If swallowed, get medical help or contact a Poison Control Center right away.

WHEN USING

Avoid contact with eyes
Do not apply to broken or severely irritated skin

Do not use on children under 2 years of age unless directed by a doctor

Stop use and ask a doctor if irritation occurs or if condition worsens

DOSAGE AND ADMINISTRATION

Clean and dry the affected area before applying
Apply a thin layer to the affected area twice daily (morning and night)
For athlete’s foot and ringworm, use daily for 4 weeks
For jock itch, use daily for 2 weeks
If condition persists longer, consult a doctor

STORAGE AND HANDLING

Store at 20°–25°C (68°–77°F)
Excursions permitted between 15°–30°C (59°–86°F)
Protect from excessive heat and direct sunlight
Do Not Freeze

INACTIVE INGREDIENT

Aloe barbadensis leaf juice, carthamus tinctorius (safflower) seed oil, petrolatum, peppermint oil, thymol, alpha-tocopherol acetate

Questions or comments?
Email romy.jean-pierre@rommyllc.com